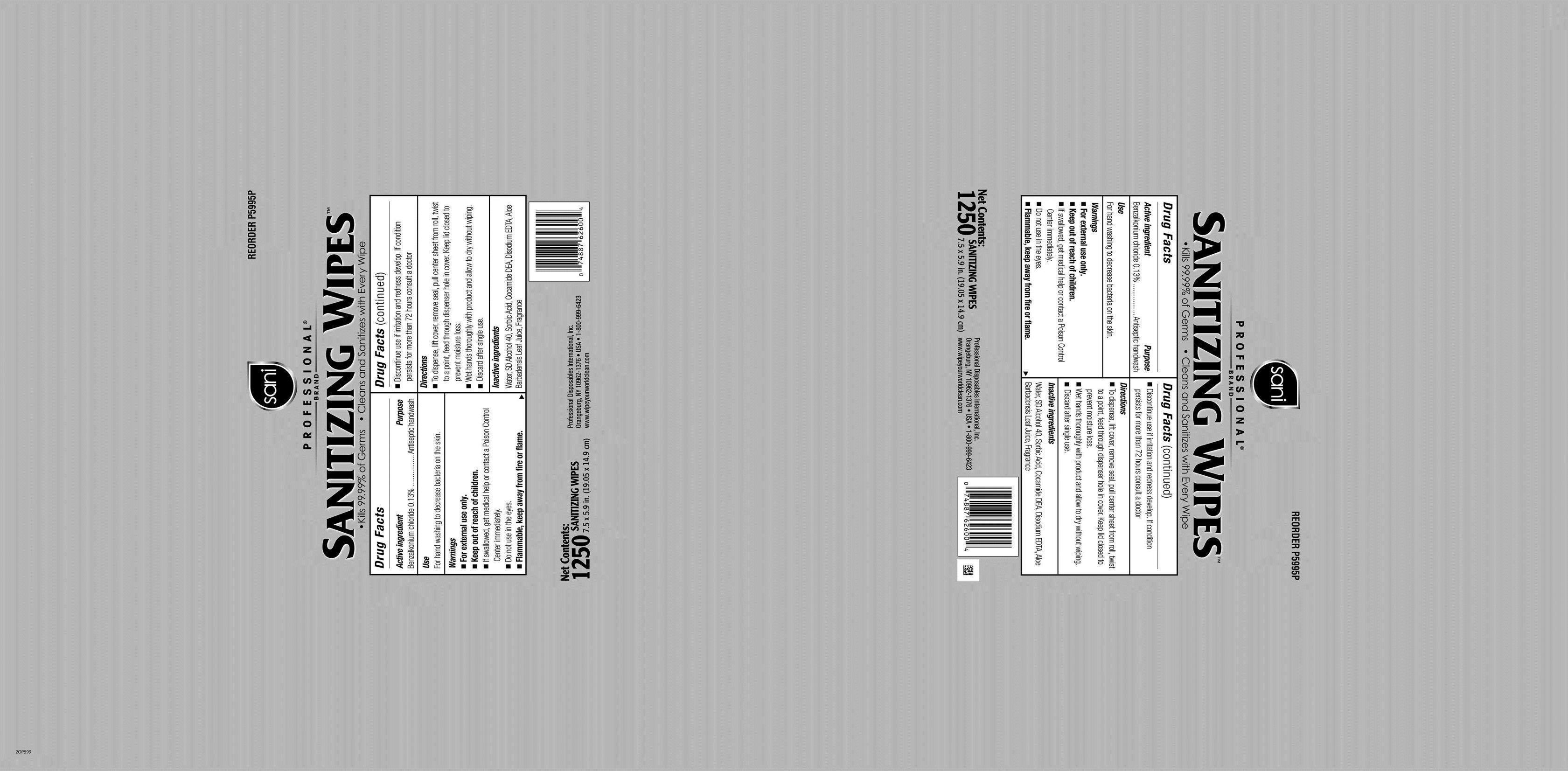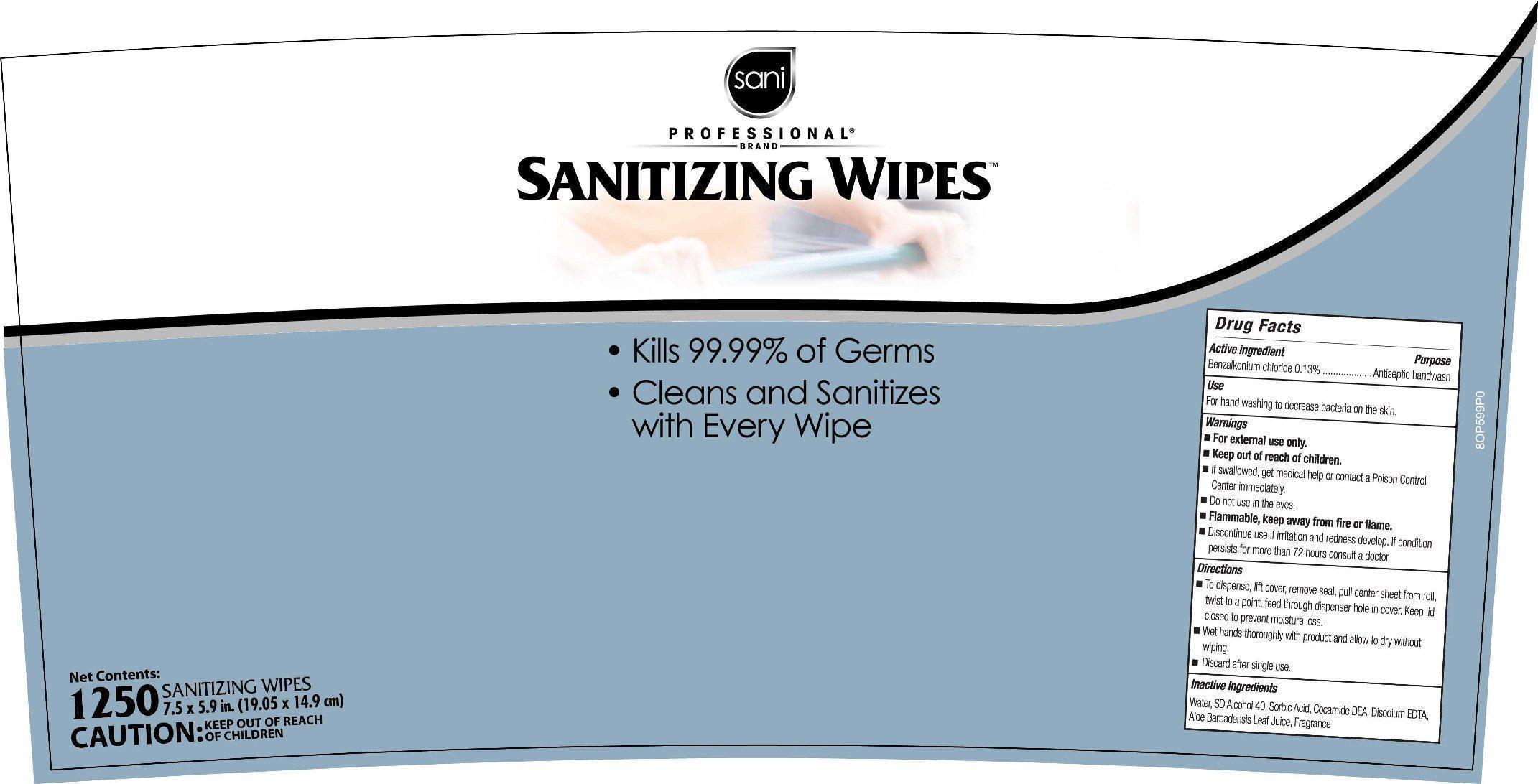 DRUG LABEL: Sani Professional Brand Sanitizing Wipes
                
NDC: 10819-7002 | Form: CLOTH
Manufacturer: Professional Disposables International, Inc.
Category: otc | Type: HUMAN OTC DRUG LABEL
Date: 20130228

ACTIVE INGREDIENTS: Benzalkonium Chloride 0.13 mg/1 mL
INACTIVE INGREDIENTS: WATER; ALCOHOL; SORBIC ACID; COCO DIETHANOLAMIDE; EDETATE DISODIUM; ALOE VERA LEAF; MICROCITRUS AUSTRALIS FRUIT

DRUG FACTS

Use

For hand washing to decrease bacteria on the skin

Warnings

- For external use only.
- If swallowed, get medical help or contact a Poison Control Center immediately.
- Do not use in the eyes.
- Flammable, keep away from fire or flame.
- Discontinue use if irritation and redness develop. If condition persists for more than 72 hours consult a doctor.

Keep out of reach of children.

Directions

- To dispense, lift cover, remove seal, pull center sheet from roll, twist to a point, feed through dispenser hole in cover. Keep lid closed to prevent moisture loss.
- Wet hands thoroughly with product and allow to dry without wiping.
- Discard after single use.

Other information

See bag label

Dosage

Wet hands thoroughly with product and allow to dry without wiping.

Inactive ingredients

Water, SD Alcohol 40, Sorbic Acid, Cocamide DEA, Disodium EDTA, Aloe Barbadensis Leaf Juice, Fragrance

Professional Disposables International, Inc.
Orangeburg, NY 10962-1376 - USA - 1-800-999-6423
Made in USA www.wipeyourworldclean.com

Principal Display Panel - 1250 Count

Sani Professional Brand
Sanitizing Wipes
Kills 99.99% of Germs
Cleans and Sanitizes with Every Wipe
1250 Sanitizing Wipes [7.5 x 5.9 in (19.05 x 14.9 cm)]
CAUTION: KEEP OUT OF REACH OF CHILDREN

Bag Label

Pail Label

Active ingredient

Benzalkonium Chloride 0.13% w/w

Purpose

Antiseptic handwash